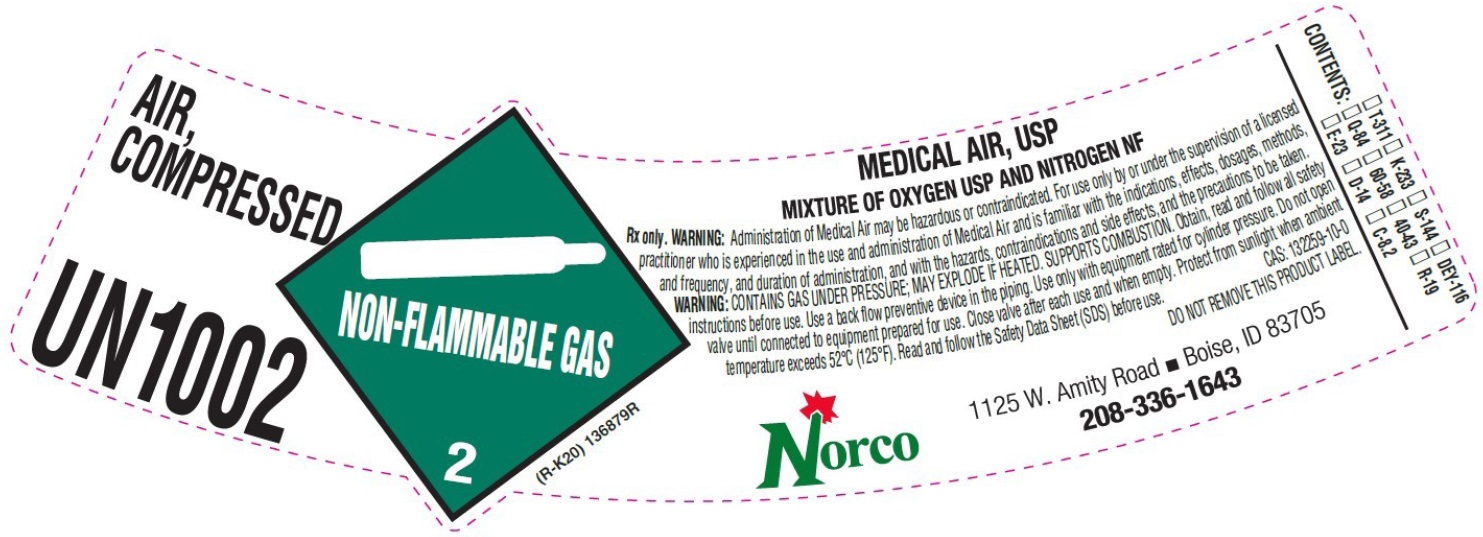 DRUG LABEL: MEDICAL AIR
NDC: 42602-004 | Form: GAS
Manufacturer: Norco, Inc.
Category: prescription | Type: HUMAN PRESCRIPTION DRUG LABEL
Date: 20250831

ACTIVE INGREDIENTS: OXYGEN 23 L/100 L
INACTIVE INGREDIENTS: NITROGEN

MEDICAL AIR USP LABEL AIR COMPRESSED

AIR, COMPRESSED USP

NON-FLAMMABLE GAS 2

(R-K20) 136879R

MIXTURE OF OXYGEN USP AND NITROGEN NF

Rx only. WARNING: Administration of Medical Air may be hazardous or contraindicated. For use only by or under the supervision of a licensed practitioner who is experienced in the use and administration of Medical Air and is familiar with the indications, effects, dosages, methods, and frequency, and duration of administration, and with the hazards, contraindications and side effects, and the precautions to be taken.

WARNING: CONTAINS GAS UNDER PRESSURE; MAY EXPLODE IF HEATED. SUPPORTS COMBUSTION. Obtain, read and follow all safety instructions before use. Use a back flow preventive device in the piping. Use only with equipment rated for cylinder pressure. Do not open valve until connected to equipment prepared for use. Close valve after each use and when empty. Protect from sunlight when ambient temperature exceeds 52º C (125º F). Read and follow Safety Data Sheet (SDS) before use. CAS: 132259-10-0
DO NOT REMOVE THIS PRODUCT LABEL.

__T-311 __K-233 __S-144 __DEY-116
__Q-84 __60-58 __40-43 __R-19
__E-23 __D-14 __C-8.2

Norco 1125 W. Amity Road • Boise, ID 83705
208-336-1643

res